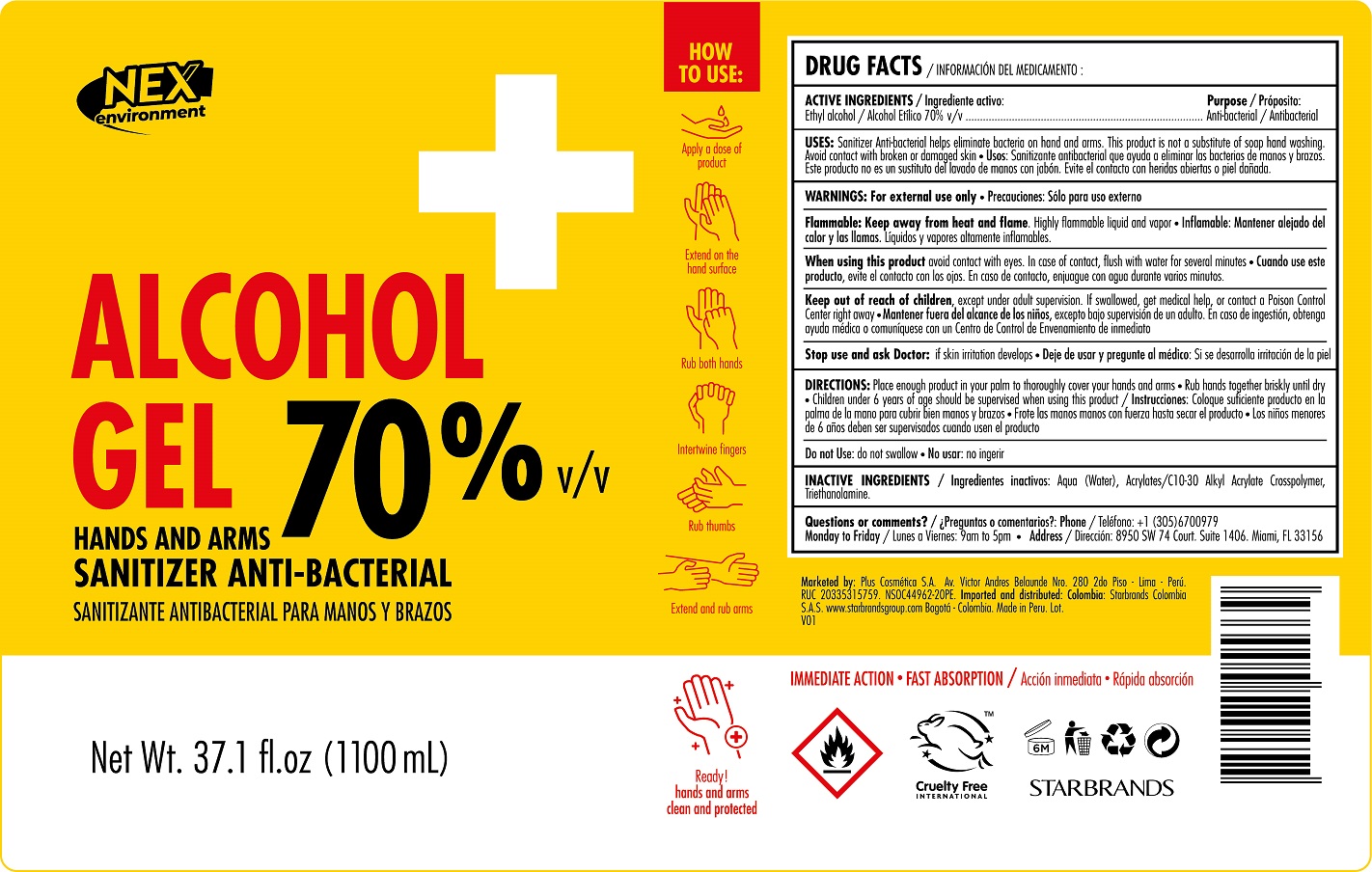 DRUG LABEL: Plus Cosmetica S A
NDC: 78343-004 | Form: GEL
Manufacturer: Plus Cosmetica S.A.
Category: otc | Type: HUMAN OTC DRUG LABEL
Date: 20200601

ACTIVE INGREDIENTS: ALCOHOL 70 mg/1 mL
INACTIVE INGREDIENTS: TROLAMINE; WATER; CARBOMER INTERPOLYMER TYPE A (ALLYL SUCROSE CROSSLINKED)

Alcohol Gel 70%

Active Ingredient

Active Ingredient Purpose

Ethyl Alcohol 70%............ Antibacterial

Uses

* Sanitizer antibacterial helps eliminate bacteria on hands and arms. This product is not a substitute of hands and soap hand washing. Avoid contact with broken or damaged skin

Warnings

- For external use only
- Flammable: Keep away from heat and flame. Highly flammable liquid and vapor.
- When using this products avoid contact with eyes. In case of contact flush with water for several minutes.
- Keep out of reach of children except under adult supervision. If swallowed, get medical help, or contact a Poison Control

Center right away.

- Stop use and ask Doctor: if skin irritation develops when using this product.
- Do not use: do not swallow

Stop use and ask a doctor if

* Irritation develops while using this product

Keep out of reach of children except under adult supervision. If swallow, get medical help or contact a Poison Center right away

Directions

- Directions: Place enough product in your palm to thoroughly cover your hands and arms. Rub hands together briskly until dry. Children under 6 years of age should be supervised when using this product.

Inactive Ingredients

water, acrylates/C10-30 Alkyl Acrylate Crosspolymer, triethanolamine

Questions?

QUESTIONS OR COMMENTS: (305) 670 0979. Monday to Friday/ Address: 8950 SW 74 Court. Suite 1406. Miami, Florida 33156

Uses

* Sanitizer antibacterial helps eliminate bacteria on hands and arms. This product is not a substitute of hands and soap hand washing. Avoid contact with broken or damaged skin